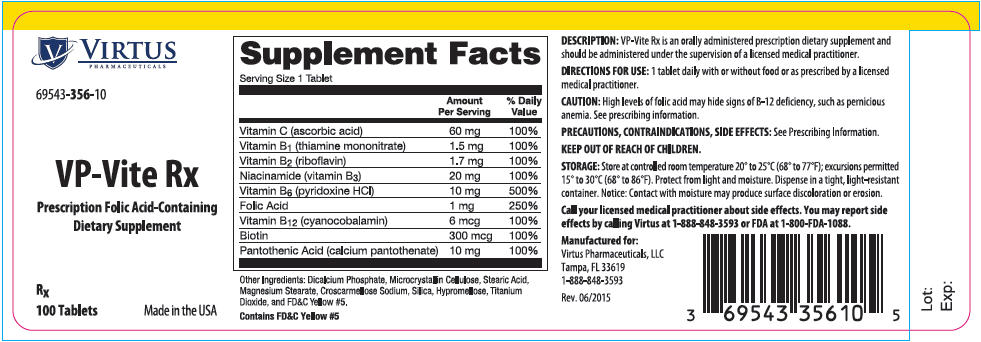 DRUG LABEL: VP-Vite Rx
NDC: 69543-356 | Form: TABLET
Manufacturer: Virtus Pharmaceuticals
Category: other | Type: DIETARY SUPPLEMENT
Date: 20150917

ACTIVE INGREDIENTS: Ascorbic Acid 60 mg/1 1; Thiamine Mononitrate 1.5 mg/1 1; Riboflavin 1.7 mg/1 1; Niacinamide 20 mg/1 1; Pyridoxine Hydrochloride 10 mg/1 1; Folic Acid 1 mg/1 1; Cyanocobalamin 6 ug/1 1; Biotin 300 ug/1 1; Calcium Pantothenate 10 mg/1 1
INACTIVE INGREDIENTS: Calcium Phosphate, Dibasic, Anhydrous; Cellulose, Microcrystalline; Stearic Acid; Magnesium Stearate; Croscarmellose Sodium; Silicon Dioxide; Hypromelloses; Titanium Dioxide; FD&C Yellow No. 5

VP-Vite Rx

HEALTH CLAIM

69543-356-10

Rx

Prescription Folic Acid-Containing Dietary Supplement

DESCRIPTION

VP-Vite Rx is an orally administered prescription dietary supplement and should be administered under the supervision of a licensed medical practitioner.

Supplement Facts
Serving Size: 1 Tablet
 | Amount Per Serving | % Daily Value
Vitamin C (ascorbic acid) | 60 mg | 100%
Vitamin B1 (thiamine mononitrate) | 1.5 mg | 100%
Vitamin B2 (riboflavin) | 1.7 mg | 100%
Niacinamide (vitamin B3) | 20 mg | 100%
Vitamin B6 (pyridoxine HCl) | 10 mg | 500%
Folic Acid | 1 mg | 250%
Vitamin B12 (cyanocobalamin) | 6 mcg | 100%
Biotin | 300 mcg | 100%
Pantothenic Acid (calcium pantothenate) | 10 mg | 100%

Other Ingredients: Dicalcium Phosphate, Microcrystalline Cellulose, Stearic Acid, Magnesium Stearate, Croscarmellose Sodium, Silica, Hypromellose, Titanium Dioxide, and FD&C Yellow #5.

Contains FD&C Yellow #5

INDICATIONS AND USAGE

VP-Vite Rx is indicated for the supplemental requirements of persons with nutritional deficiencies or those who are in need of nutritional supplementation.

CONTRAINDICATIONS

This product is contraindicated in persons with a known hypersensitivity to any of the ingredients.

PRECAUTIONS

High levels of folic acid may, especially in older adults, hide signs of vitamin B-12 deficiency (such as pernicious anemia, a condition that can cause nerve damage).

PATIENT INFORMATION

VP-Vite Rx is a prescription vitamin for use only under the direction and supervision of a licensed physician.

DRUG INTERACTIONS

Pyridoxine hydrochloride should not be given to patients receiving the drug levodopa, because the action of levodopa is antagonized by pyridoxine hydrochloride. However, pyridoxine hydrochloride may be used concurrently in patients receiving a preparation containing both carbidopa and levodopa.

Drugs which may interact with folate include:

- Antiepileptic drugs (AED): The AED class including, but not limited to, phenytoin, carbamazepine, primidone, valproic acid, phenobarbital and lamotrigine have been shown to impair folate absorption and increase the metabolism of circulating folate. Additionally, concurrent use of folic acid has been associated with enhanced phenytoin metabolism, lowering the levels of this AED in the blood and allowing breakthrough seizures to occur.
- Capecitabine: Folinic acid (5-formyltetrahydrofolate) may increase the toxicity of Capecitabine.
- Cholestyramine: Reduces folic acid absorption and reduces serum folate levels.
- Colestipol: Reduces folic acid absorption and reduces serum folate levels.
- Cycloserine: Reduces folic acid absorption and reduces serum folate levels.
- Dihydrofolate Reductase Inhibitors (DHFRI): DHFRIs including aminopterin, methotrexate, pyrimethamine, triamterene, and trimethoprim, block the conversion of folic acid to its active forms, and lower plasma and red blood cell folate levels.
- Fluoxetine: Fluoxetine exerts a noncompetitive inhibition of 5-methyltetrahydrofolate active transport in the intestine.
- Isotretinoin: Reduced folate levels have occurred in some patients taking isotretinoin.
- Nonsteroidal Anti-inflammatory Drugs (NSAIDs): NSAIDs, including ibuprofen, naproxen, indomethacin and sulindac, have been shown to inhibit some folate-dependent enzymes in laboratory experiments.
- Oral Contraceptives: Serum folate levels may be depressed by oral contraceptive therapy.
- Methylprednisolone: Reduced serum folate levels have been noted after treatment with methylprednisolone.
- Pancreatic Enzymes: Reduced folate levels have occurred in some patients taking pancreatic extracts.
- Pentamidine: Reduced folate levels have been seen with prolonged intravenous pentamidine treatment.
- Smoking and alcohol: Reduced serum folate levels have been noted.
- Sulfasalazine: Inhibits the absorption and metabolism of folic acid.
- Metformin treatment in patients with type 2 diabetes decreases serum folate.
- Warfarin can produce significant impairment in folate status after a 6-month therapy.

SIDE EFFECTS

Allergic sensitization has been reported following oral administration of folic acid. Paresthesia, somnolence, nausea and headaches have been reported with pyridoxine hydrochloride. Mild transient diarrhea, polycythemia vera, itching, transitory exanthema and the feeling of swelling of the entire body have been associated with cyanocobalamin.

DIRECTIONS FOR USE

1 tablet daily with or without food or as prescribed by a licensed medical practitioner.

HOW SUPPLIED

VP-Vite Rx Supplied as round, yellow tablet imprinted with "V356" dispensed in 100 count bottles.

69543-356-10

STORAGE

Store at 20° to 25°C (68° to 77°F), excursions permitted to 15° to 30°C (59° to 86°F) Protect from light and moisture. Dispense in a tight, light-resistant container. Notice: Contact with moisture may produce surface discoloration or erosion.

HEALTH CLAIM

Call your licensed medical practitioner about side effects. You may report side effects by calling Virtus at 1-888-848-3593 or FDA at 1-800-FDA-1088.

KEEP OUT OF REACH OF CHILDREN

Rx

Manufactured for:
Virtus Pharmaceuticals, LLC
Tampa, FL 33619
1-888-848-3593

Rev. 06/15

PRINCIPAL DISPLAY PANEL - 100 Tablet Bottle Label

VIRTUS
PHARMACEUTICALS

69543-356-10

VP-Vite Rx

Prescription Folic Acid-Containing
Dietary Supplement

Rx
100 Tablets
Made in the USA